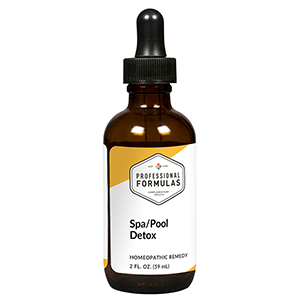 DRUG LABEL: Spa/Pool Detox
NDC: 63083-6027 | Form: LIQUID
Manufacturer: Professional Complementary Health Formulas
Category: homeopathic | Type: HUMAN OTC DRUG LABEL
Date: 20190815

ACTIVE INGREDIENTS: SODIUM CARBONATE 12 [hp_X]/59 mL; CHLORINE 12 [hp_X]/59 mL; CUPRIC CATION 30 [hp_X]/59 mL; BROMINE 30 [hp_X]/59 mL; AMMONIUM CATION 30 [hp_X]/59 mL; SODIUM CATION 30 [hp_X]/59 mL; ETIDRONIC ACID 30 [hp_X]/59 mL; CRYPTOSPORIDIUM HOMINIS 30 [hp_X]/59 mL; ESCHERICHIA COLI 30 [hp_X]/59 mL
INACTIVE INGREDIENTS: ALCOHOL; WATER

X27

ACTIVE INGREDIENTS

Sodium carbonate 12X
Pool water 12X, 30X, 60X
Spa water 12X, 30X, 60X
Algaecide 30X
Brominating tablets 30X
Bromium 30X
Clarifier 30X
Chlorinum 30X
Spa oxidizer 30X
Spa stain/scale 30X
Sodium bisulfate 30X
Cryptosporidium 30X, 60X, 100X
Escherichia coli 30X, 60X, 100X

QUESTIONS

Professional Formulas

PO Box 2034 Lake Oswego, OR 97035

INDICATIONS

For the temporary relief of skin irritations, red or watery eyes, minor earache, stomach cramps, diarrhea, or vomiting due to sensitivity to or exposure to pool or spa chemicals or contaminants.*

PURPOSE

*Claims based on traditional homeopathic practice, not accepted medical evidence. Not FDA evaluated.

WARNINGS

Consult a doctor if condition worsens or symptoms persist. Keep out of the reach of children. In case of overdose, get medical help or contact a poison control center right away. If pregnant or breastfeeding, ask a healthcare professional before use.

Keep out of the reach of children.

PREGNANCY OR BREAST FEEDING

If pregnant or breastfeeding, ask a healthcare professional before use.

DIRECTIONS

Place drops under tongue 30 minutes before/after meals. Adults and children 12 years and over: Take 10 drops up to 3 times per day. Consult a physician for use in children under 12 years of age.

OTHER INFORMATION

Tamper resistant. If seal is broken, do not use. After opening, close container tightly and store at room temperature away from heat.

INACTIVE INGREDIENTS

20% ethanol, purified water.

LABEL

Est 1985

Professional Formulas

Complementary Health

Spa/Pool Detox

Homeopathic Remedy

2 FL. OZ. (59 mL)